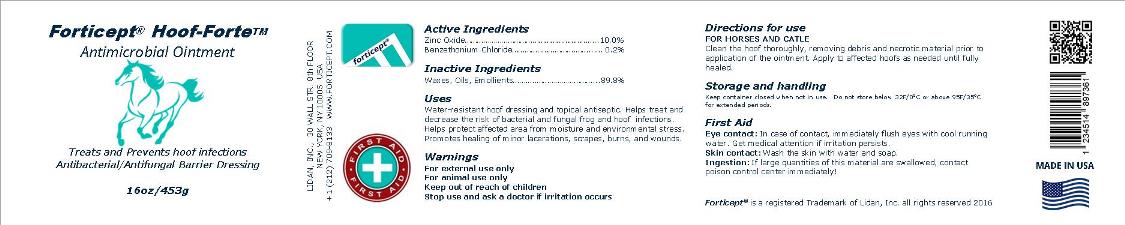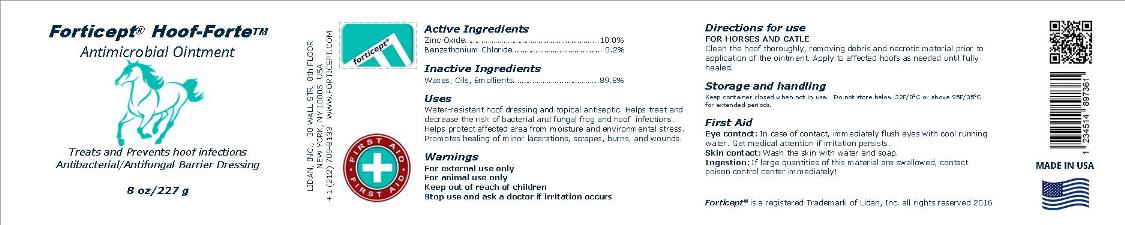 DRUG LABEL: Forticept Hoof-Forte
NDC: 72127-0705 | Form: OINTMENT
Manufacturer: Lidan, inc.
Category: animal | Type: OTC ANIMAL DRUG LABEL
Date: 20240927

ACTIVE INGREDIENTS: ZINC OXIDE .1 kg/1 kg; BENZETHONIUM CHLORIDE 0.002 kg/1 kg

FORTICEPT HOOF-FORTE ANTIMICROBIAL OUNTMENT

DRUG FACTS

Active Ingredients:

Zinc Oxide………………….....................10.0%
Benzethonium Chloride.....................0.2%

Inactive Ingredients:

Waxes, Oils, Emollients………………... 89.8%

Uses:

Water-resistant hoof dressing and topical antiseptic.

INDICATIONS AND USAGE

Helps treat and decrease the risk of bacterial and fungal frog and hoof infections. Helps protect affected area from moisture and environmental stress. Promotes healing of minor lacerations, scrapes, burns, and wounds.

Warnings:

• For external use only
• For animal use only

• Keep out of reach of children

• When using this product - avoid eye contact

Directions for use:

FOR HORSES AND CATLE
Clean the hoof thoroughly, removing debris and necrotic material prior to application of the ointment. Apply to affected hoofs as needed until fully healed.

Storage and handling:

Keep container closed when not in use. Do not store below 32F/00C or above 95F/350C for extended periods.

FIRST AID

Eye contact: In case of contact, immediately flush eyes with cool running water. Get medical attention if irritation persists.
Skin contact: Wash the skin with water and soap.
Ingestion: If large quantities of this material are swallowed, contact poison control center immediately!

For questions, please call: +1 212 709-8133